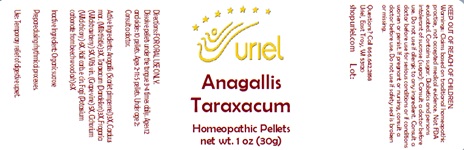 DRUG LABEL: Anagallis Taraxacum
NDC: 48951-1031 | Form: PELLET
Manufacturer: Uriel Pharmacy Inc.
Category: homeopathic | Type: HUMAN OTC DRUG LABEL
Date: 20241218

ACTIVE INGREDIENTS: ANAGALLIS ARVENSIS 3 [hp_X]/1 1; MILK THISTLE 3 [hp_X]/1 1; TARAXACUM PALUSTRE ROOT 3 [hp_X]/1 1; FRAGARIA VESCA WHOLE 5 [hp_X]/1 1; VITIS VINIFERA LEAF 5 [hp_X]/1 1; CICHORIUM INTYBUS WHOLE 6 [hp_X]/1 1; POTASSIUM CARBONATE 6 [hp_X]/1 1
INACTIVE INGREDIENTS: SUCROSE

Anagallis Taraxacum

INDICATIONS AND USAGE

Directions: FOR ORAL USE ONLY.

DOSAGE AND ADMINISTRATION

Dissolve pellets under the tongue 3-4 times daily. Ages 12 and older: 10 pellets. Ages 2-11: 5 pellets. Under age 2: Consult a doctor.

ACTIVE INGREDIENT

Active Ingredients: Anagallis (Scarlet pimpernel) 3X, Carduus mar. (Milk thistle) 3X, Taraxacum (Dandelion) 3X, Fragaria (Wild strawberry) 5X, Vitis vin. (Grape vine) 5X, Cichorium (Wild chicory) 6X, Kali carb. e cin. Fagi (Potassium carbonate from beech wood ash) 6X

Inactive Ingredient: Organic sucrose

Prepared using rhythmical processes.

PURPOSE

Use: Temporary relief of digestive upset.

KEEP OUT OF REACH OF CHILDREN.

WARNINGS

Warnings: Claims based on traditional homeopathic practice, not accepted medical evidence. Not FDA evaluated. Contains sugar. Diabetics and persons intolerant of sucrose (sugar): Consult a doctor before use. Do not use if allergic to any ingredient. Consult a doctor before use for serious conditions or if conditions worsen or persist. If pregnant or nursing, consult a doctor before use. Do not use if safety seal is broken or missing.

QUESTIONS

Questions? Call 866.642.2858 Uriel, East Troy, WI 53120 shopuriel.com Lot: